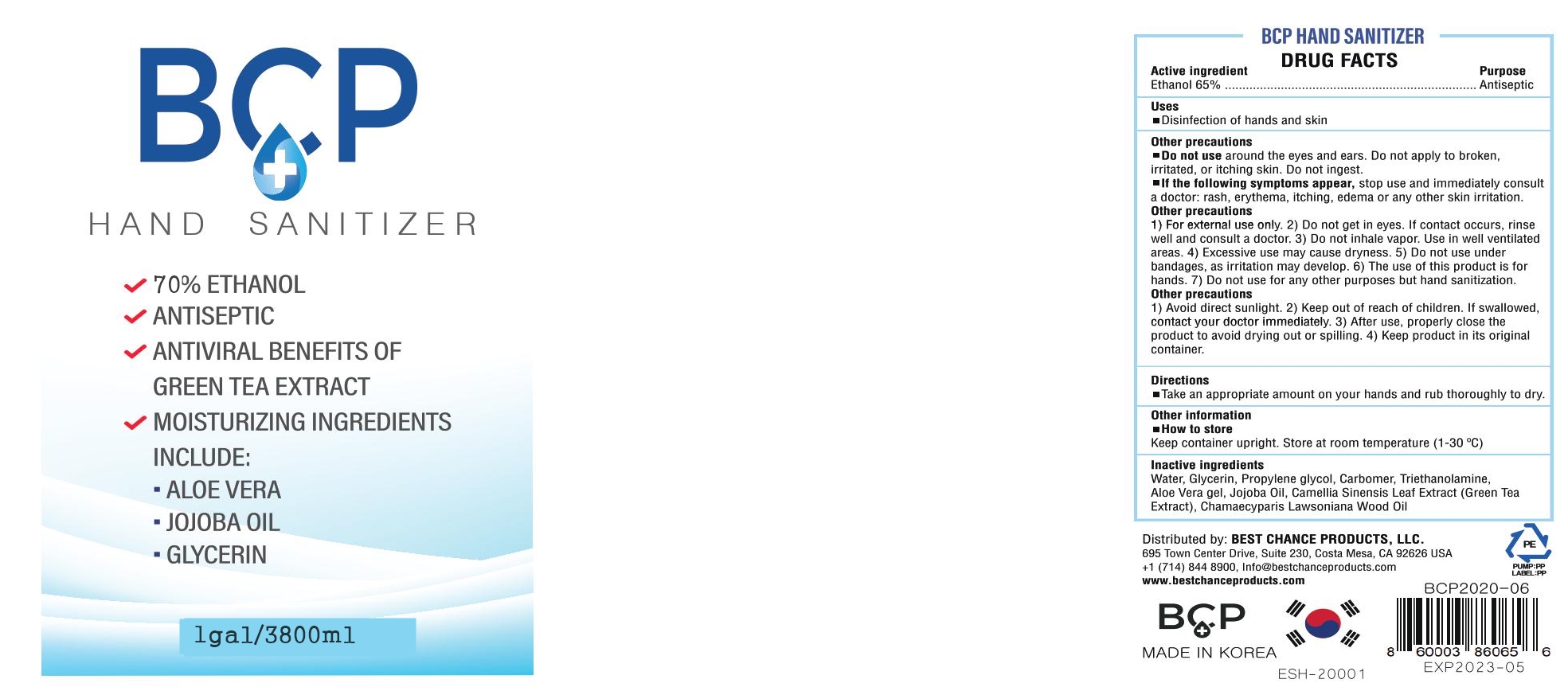 DRUG LABEL: BCP HAND SANITIZER
NDC: 78252-302 | Form: GEL
Manufacturer: Best Chance Products, LLC
Category: otc | Type: HUMAN OTC DRUG LABEL
Date: 20200615

ACTIVE INGREDIENTS: ALCOHOL 70 mL/100 mL
INACTIVE INGREDIENTS: PROPYLENE GLYCOL 0.2 mL/100 mL; JOJOBA OIL 0.02 mL/100 mL; GREEN TEA LEAF 0.02 mL/100 mL; TROLAMINE 0.2 mL/100 mL; CHAMAECYPARIS LAWSONIANA WOOD OIL 0.01 mL/100 mL; CARBOMER 940 0.2 mL/100 mL; ALOE VERA LEAF 0.02 mL/100 mL; WATER 29.13 mL/100 mL; GLYCERIN 0.2 mL/100 mL

Sanitizer

Active Ingredient

alchol70%

PURPOSE

Antiseptic

inactive ingredient

ALCOHOL, JOJOBA OIL, GREEN TEA LEAF
GLYCERIN, CHAMAECYPARIS LAWSONIANA WOOD OIL , CARBOMER
ALOE VERA LEAF , WATER , PROPYLENE GLYCOL ,TROLAMINE

Direction

Take an appropriate amount on your hands and rub thoroughly to dry.

for external use only

Do not use

around the eyes ane ears. Do not apply to broken irritated, or itching skin.Do not ingest.

Use

Hand sanitizer to help reduce bacteria that potentially can cause disease.
For use when soap and water are not avaliable.

Warnings

for external use only.

Do not get in eyes. do not inhale vapor.

do not use under bandages, as irritation may develop.

do not use for any other purpose but hands sanitization.

Keep out of reach of children.

If swallowed contact your doctor immediately

Stop use and ask a doctor.

if the following symptoms appear,Stop use and immediately consult a doctor: rash, erythema, itching, edema or any other skin irritation.

Other information

keep container upright. Store at room temperature (1-30'C)

indication

After use, properly close the product to avoid drying out or spilling.

Take an appropriate amount on your hands and rub thoroughly to dry.

pakage label

78252-302-01